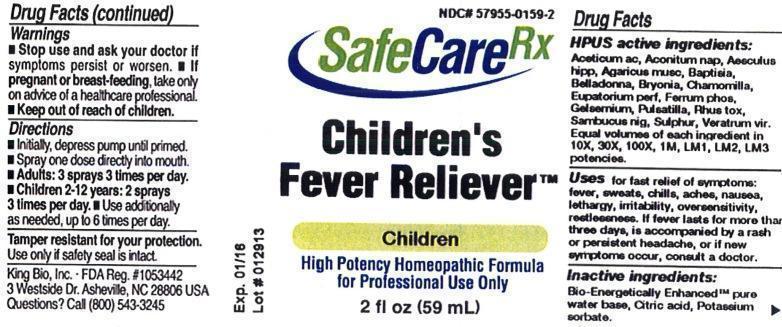 DRUG LABEL: Childrens Fever Reliever
NDC: 57955-0159 | Form: LIQUID
Manufacturer: King Bio Inc.
Category: homeopathic | Type: HUMAN PRESCRIPTION DRUG LABEL
Date: 20130416

ACTIVE INGREDIENTS: ACETIC ACID 10 [hp_X]/59 mL; ACONITUM NAPELLUS 10 [hp_X]/59 mL; HORSE CHESTNUT 10 [hp_X]/59 mL; AMANITA MUSCARIA VAR. MUSCARIA FRUITING BODY 10 [hp_X]/59 mL; BAPTISIA TINCTORIA ROOT 10 [hp_X]/59 mL; ATROPA BELLADONNA 10 [hp_X]/59 mL; BRYONIA ALBA ROOT 10 [hp_X]/59 mL; MATRICARIA RECUTITA 10 [hp_X]/59 mL; EUPATORIUM PERFOLIATUM FLOWERING TOP 10 [hp_X]/59 mL; FERROSOFERRIC PHOSPHATE 10 [hp_X]/59 mL; GELSEMIUM SEMPERVIRENS ROOT 10 [hp_X]/59 mL; PULSATILLA VULGARIS 10 [hp_X]/59 mL; TOXICODENDRON PUBESCENS LEAF 10 [hp_X]/59 mL; SAMBUCUS NIGRA FLOWERING TOP 10 [hp_X]/59 mL; SULFUR 10 [hp_X]/59 mL; VERATRUM VIRIDE ROOT 10 [hp_X]/59 mL
INACTIVE INGREDIENTS: WATER; CITRIC ACID MONOHYDRATE; POTASSIUM SORBATE

Childrens Fever Reliever

Warnings

- Stop use and ask your doctor if symptoms persist or worsen.
- If pregnant or breast-feeding, take only on advice of a healthcare professional.
- Keep out of reach of children.

Tamper resistant for your protection. Use only if safety seal is intact.

Keep out of reach of children

Dosage and Administration

- Initially, depress pump until primed.
- Spray one dose directly into mouth.
- Adults: 3 sprays 3 times per day.
- Children 2-12 years: 2 sprays 3 times per day.
- Use additionally as needed, up to 6 times per day.

HPUS Active Ingredients

Aceticum acidum, Aconitum napellus, Aesculus hippocastanum, Agaricus muscarius, Baptisia tinctoria, Belladonna, Bryonia, Chamomilla, Eupatorium perfoliatum, Ferrum phosphoricum, Gelsemium sempervirens, Pulsatilla, Rhus toxicodendron, Sambucus nigra, Sulphur, Veratrum Viride. Equal volumes of each ingredient in 10X, 30X, 100X, 1M, LM1, LM2, LM3 potencies.

Purpos

Uses for fast relief of symptoms:

- fever
- sweats
- chills
- aches
- nausea
- lethargy
- irritability
- oversensitivity
- restlessness

If fever lasts for more than three days, is accompanied by a rash or persistent headache, or if new symptoms occur, consult a doctor.

Inactive ingredients

Bio-Energetically Enhanced™ pure water base, Citric acid and Potassium sorbate.

Indications and Usage

Uses for fast relief of symptoms: fever, sweats, chills, aches, nausea, lethargy, irritability, oversensitivity, restlessness. If fever lasts for more than three days, is accompanied by a rash or persistent headache, or if new symptoms occur, consult a doctor.